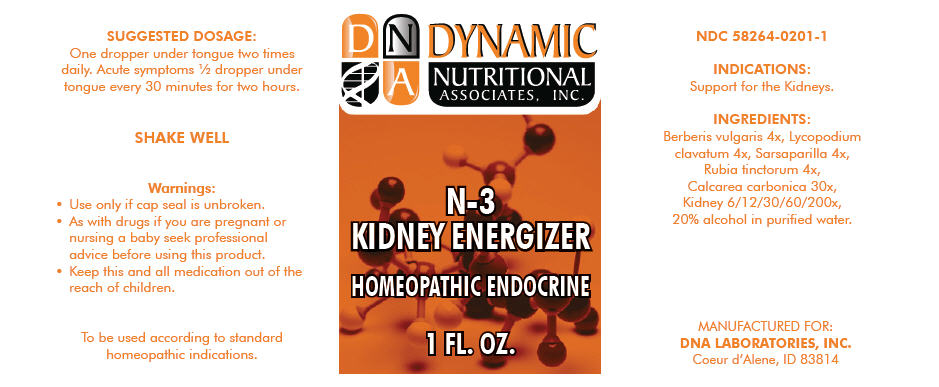 DRUG LABEL: N-3
NDC: 58264-0201 | Form: SOLUTION
Manufacturer: DNA Labs, Inc.
Category: homeopathic | Type: HUMAN OTC DRUG LABEL
Date: 20250109

ACTIVE INGREDIENTS: BERBERIS VULGARIS WHOLE 4 [hp_X]/1 mL; LYCOPODIUM CLAVATUM WHOLE 4 [hp_X]/1 mL; SMILAX ORNATA WHOLE 4 [hp_X]/1 mL; RUBIA TINCTORUM WHOLE 4 [hp_X]/1 mL; OYSTER SHELL CALCIUM CARBONATE, CRUDE 30 [hp_X]/1 mL; PORK KIDNEY 200 [hp_X]/1 mL
INACTIVE INGREDIENTS: ALCOHOL; WATER

N-3

NDC 58264-0201-1

INDICATIONS

PURPOSE

Support for the Kidneys.

INGREDIENTS

INACTIVE INGREDIENT

Berberis vulgaris 4x, Lycopodium clavatum 4x, Sarsaparilla 4x, Rubia tinctorum 4x, Calcarea carbonica 30x, Kidney 6/12/30/60/200x, 20% alcohol in purified water.

SUGGESTED DOSAGE

One dropper under tongue two times daily. Acute symptoms ½ dropper under tongue every 30 minutes for two hours.

STORAGE AND HANDLING

SHAKE WELL

Warnings

- Use only if cap seal is unbroken.

PREGNANCY OR BREAST FEEDING

- As with drugs if you are pregnant or nursing a baby seek professional advice before using this product.

KEEP OUT OF REACH OF CHILDREN

- Keep this and all medication out of the reach of children.

To be used according to standard homeopathic indications.

PRINCIPAL DISPLAY PANEL - 1 FL. OZ. Bottle Label

DYNAMIC
NUTRITIONAL
ASSOCIATES, INC.

N-3
KIDNEY ENERGIZER

HOMEOPATHIC ENDOCRINE

1 FL. OZ.